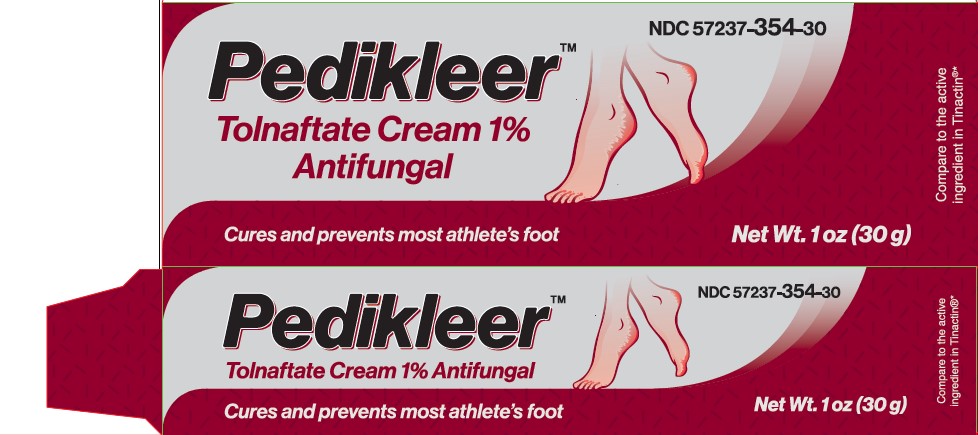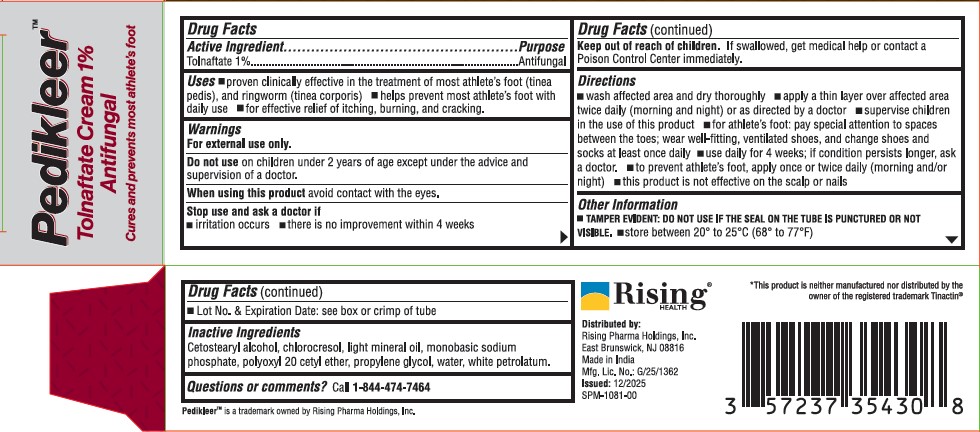 DRUG LABEL: Pedikleer
NDC: 57237-354 | Form: CREAM
Manufacturer: Rising Pharma Holdings, Inc.
Category: otc | Type: HUMAN OTC DRUG LABEL
Date: 20251211

ACTIVE INGREDIENTS: TOLNAFTATE 1 g/100 g
INACTIVE INGREDIENTS: CETOSTEARYL ALCOHOL; CHLOROCRESOL; LIGHT MINERAL OIL; SODIUM PHOSPHATE, MONOBASIC; POLYOXYL 20 CETOSTEARYL ETHER; PROPYLENE GLYCOL; WATER; WHITE PETROLATUM

Pedikleer
Tolnaftate Cream 1% Antifungal

Drug Facts Active Ingredient

Tolnaftate 1%

Purpose

Antifungal

Uses

- proven clinically effective in the treatment of most athlete's foot (tinea pedis), and ringworm (tinea corporis)
- helps prevent most athlete's foot with daily use
- for effective relief of itching, burning, and cracking.

Warnings

For external use only.

Do not use on children under 2 years of age except under the advice and supervision of a doctor.

When using this product avoid contact with the eyes.

Stop use and ask a doctor if

- irritation occurs
- there is no improvement within 4 weeks

Keep out of reach of children. If swallowed, get medical help or contact a Poison Control Center immediately.

Directions

- wash affected area and dry thoroughly
- apply a thin layer over affected area twice daily (morning and night) or as directed by a doctor
- supervise children in the use of this product
- for athlete's foot: pay special attention to spaces between the toes; wear well-fitting, ventilated shoes, and change shoes and socks at least once daily
- use daily for 4 weeks; if condition persists longer, ask a doctor.
- to prevent athlete's foot, apply once or twice daily (morning and/or night)
- this product is not effective on the scalp or nails

Other Information

- TAMPER EVIDENT: DO NOT USE IF THE SEAL ON THE TUBE IS PUNCTURED OR NOT VISIBLE.
- store between 20º to 25ºC (68º to 77ºF)
- Lot No. & Expiration Date: see box or crimp of tube

Inactive Ingredients

Cetostearyl alcohol, chlorocresol, light mineral oil, monobasic sodium phosphate, polyoxyl 20 cetyl ether, propylene glycol, water, white petrolatum.

Questions or comments?

Call 1-844-474-7464

PACKAGE LABEL

Distributed by:
Rising Pharma Holdings, Inc.
East Brunswick, NJ 08816
Made in India
Mfg. Lic. No.: G/25/1362
Issued: 12/2025